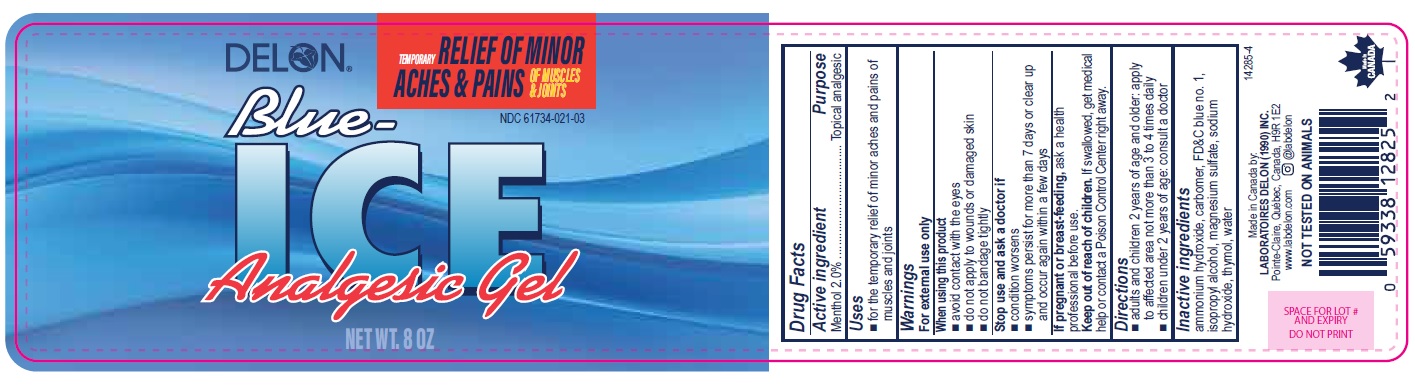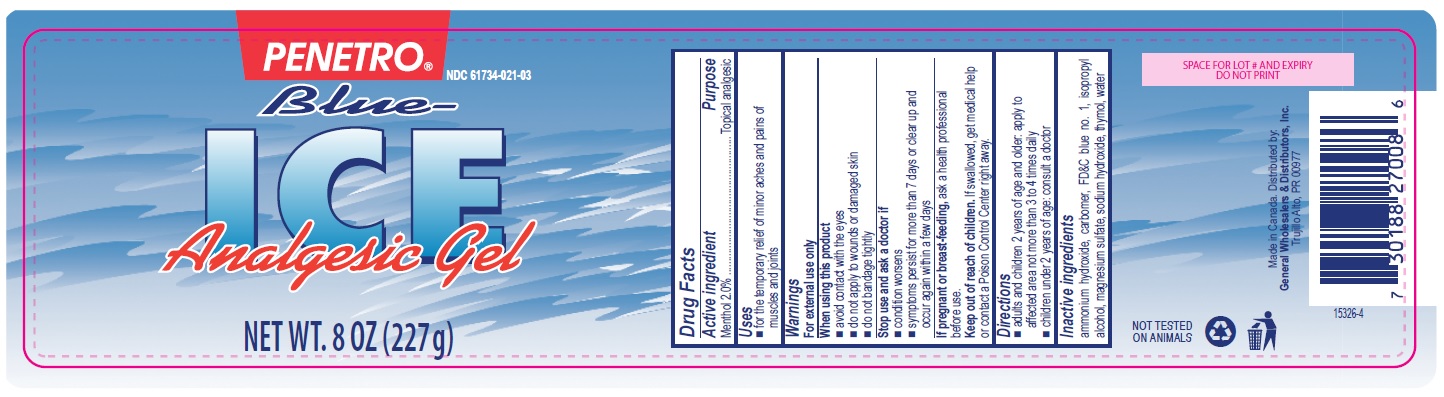 DRUG LABEL: Blue Ice Analgesic
NDC: 61734-021 | Form: GEL
Manufacturer: Delon Laboratories (1990) Ltd
Category: otc | Type: HUMAN OTC DRUG LABEL
Date: 20251016

ACTIVE INGREDIENTS: MENTHOL 2 g/100 g
INACTIVE INGREDIENTS: THYMOL; AMMONIA; SODIUM HYDROXIDE; MAGNESIUM SULFATE HEPTAHYDRATE; CARBOMER 934; FD&C BLUE NO. 1; WATER; ISOPROPYL ALCOHOL

Blue Ice Gel

Active ingredient

Menthol 2.0%

Purpose

Topical analgesic

Uses

- for the temporary relief of minor aches and pains of muscles and joints

Warnings

For external use only

When using this product

- avoid contact with the eyes
- do not apply to wounds or damaged skin
- do not bandage tightly

Stop use and ask a doctor if

- condition worsens
- symptoms persist for more than 7 days or clear up and occur again within a few days

PREGNANCY OR BREAST FEEDING

If pregnant or breast-feeding, ask a health professional before use.

Keep out of reach of children. If swallowed, get medical help or contact a Poison Control Center right away.

Directions

- adults and children 2 years of age and older: apply to affected area not more than 3 to 4 times daily
- children under 2 years of age: consult a doctor

Inactive ingredients

ammonium hydroxide, carbomer, FD&C blue no. 1, isopropyl alcohol, magnesium sulfate, sodium hydroxide, thymol, water